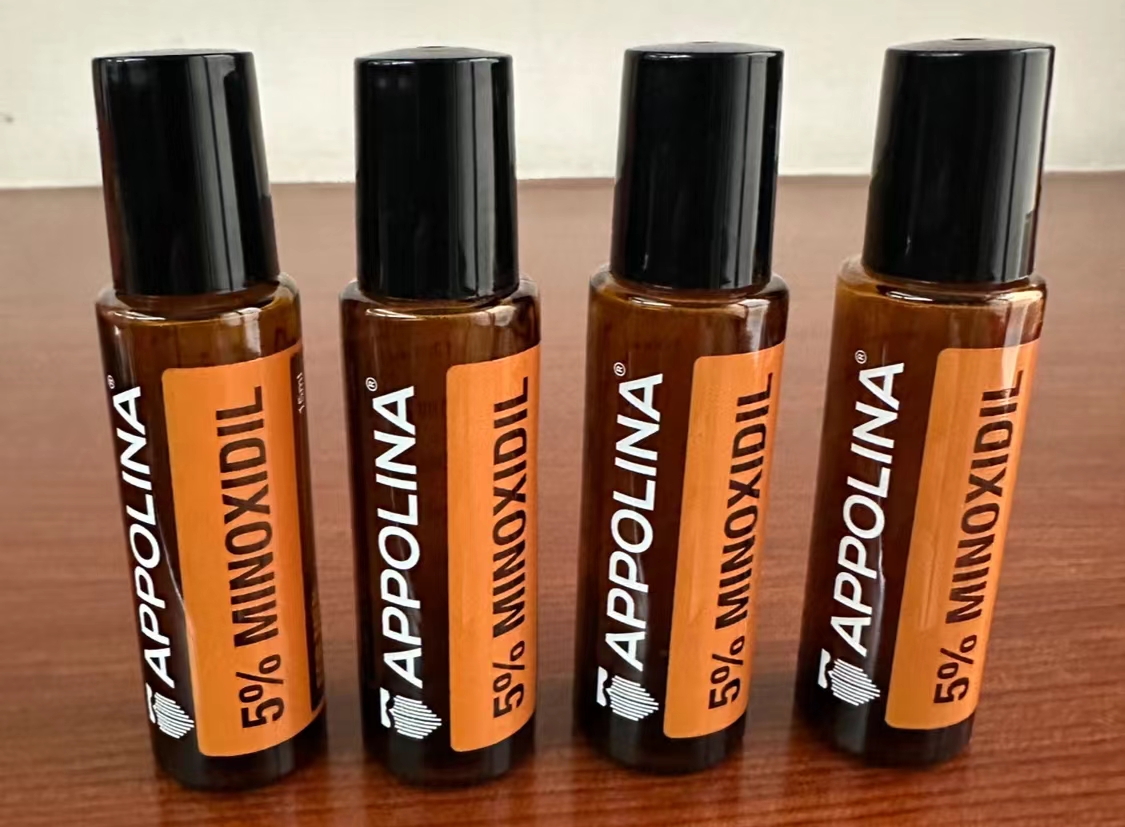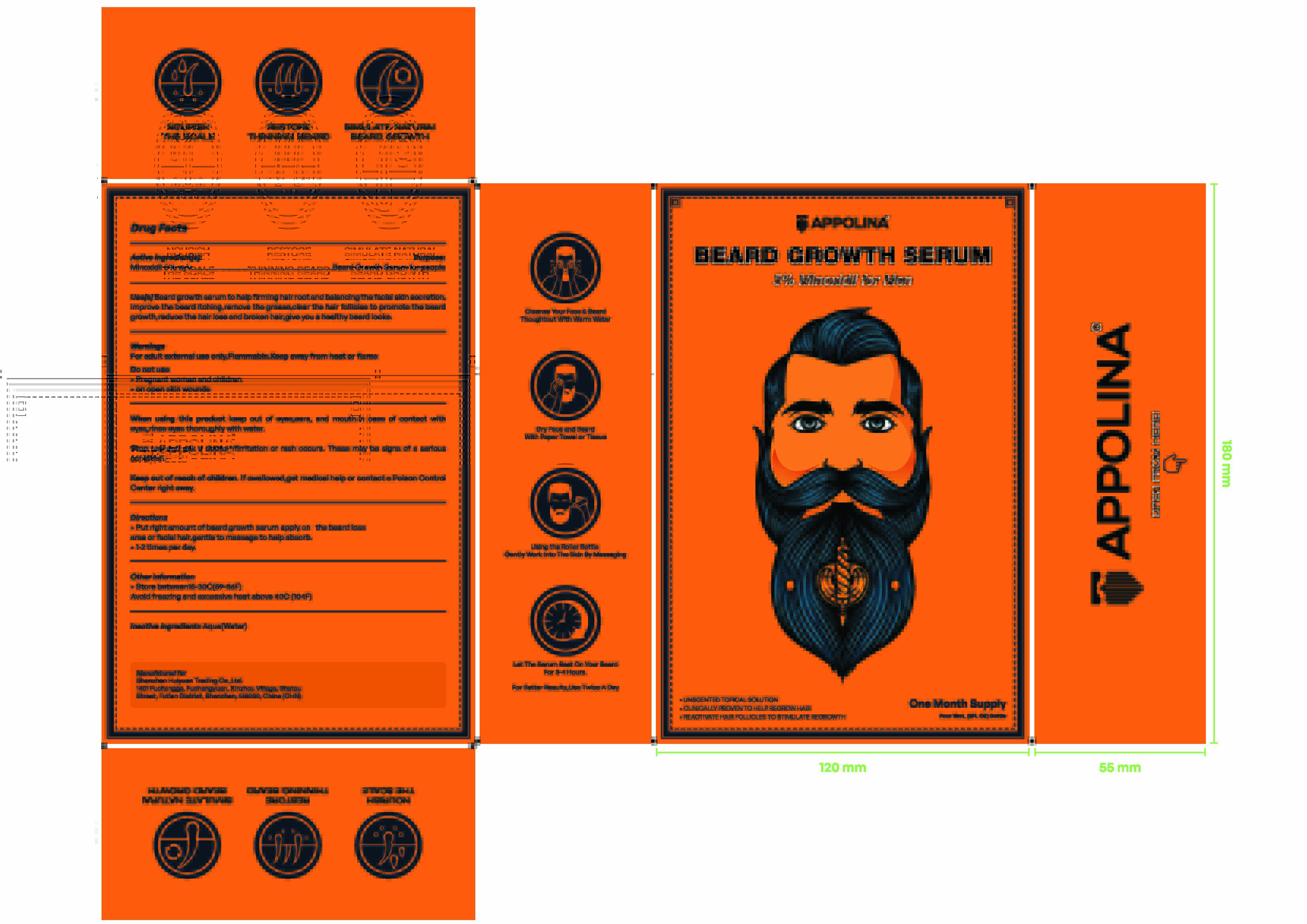 DRUG LABEL: 5% MINOXIDIL BEARD GROWTH SERUM
NDC: 84183-101 | Form: LIQUID
Manufacturer: Shenzhen Huiyuan Trading Co., Ltd.
Category: otc | Type: HUMAN OTC DRUG LABEL
Date: 20250108

ACTIVE INGREDIENTS: MINOXIDIL 5 g/100 mL
INACTIVE INGREDIENTS: WATER

5% MINOXIDIL BEARD GROWTH SERUM

5% MINOXIDIL BEARD GROWTH SERUM

ACTIVE INGREDIENT

5% minoxidil

PURPOSE

Beard Growth Serum for people

INDICATIONS AND USAGE

Use[s] Beard growth serum to help firming hair root and balancing the facial skin secretion,improve the beard itching,remove the grease,clear the hair follicles to promote the beardgrowth,reduce the hair loss and broken hair,give you a healthy beard looks.

WARNINGS

For adult external use only.Flammable.Keep away from heat or flame

DO NOT USE

Pregnant women and children
on open skin wounds

WHEN USING

eyes,ears, and mouth.ln case of contact with eyes,rinse eyes thoroughly with water.

Stop use and ask a doctor ifirritation or rash occurs. These may be signs of a serious condition.

KEEP OUT OF REACH OF CHILDREN

lf swallowed,get medical help or contact a Poison Control Center right away.

DOSAGE AND ADMINISTRATION

Put right amount of beard growth serum apply on the beard loss area or facial hair,gentle to massage to help absorb.
1-2 times per day.

STORAGE AND HANDLING

Store between15-30C(59-86F)

Avoid freezing and excessive heat above 40C (104F)

INACTIVE INGREDIENT

WATER